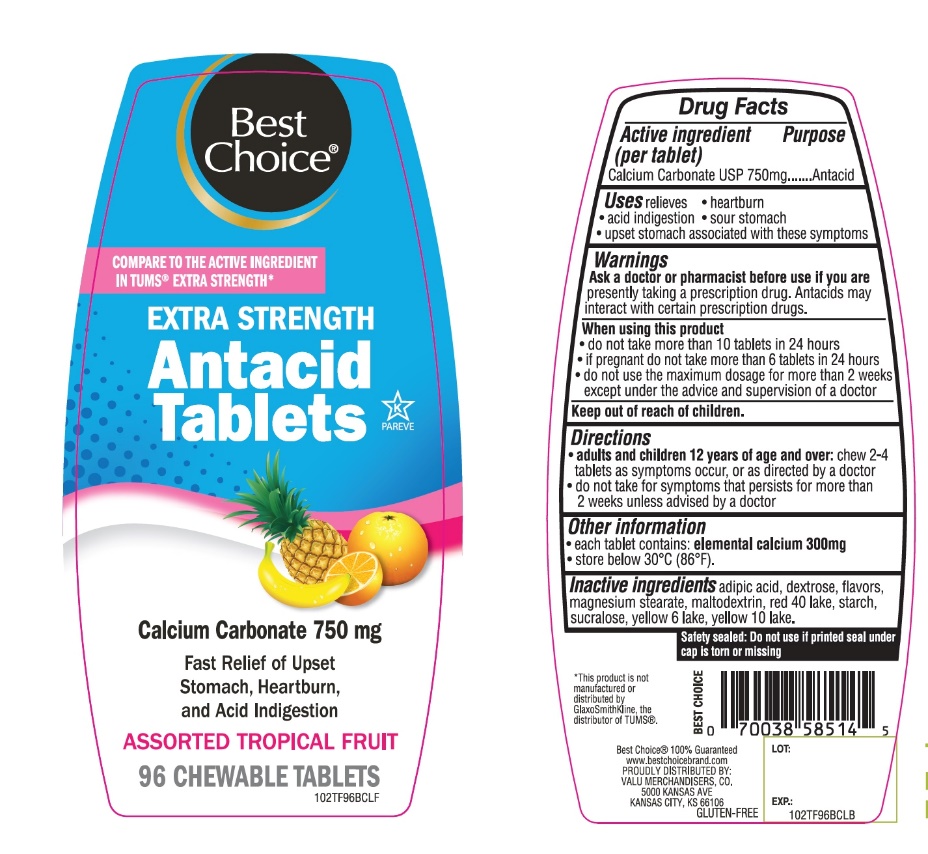 DRUG LABEL: Best Choice Extra Strength

NDC: 63941-022 | Form: TABLET, CHEWABLE
Manufacturer: BEST CHOICE (VALU MERCHANDISERS COMPANY)
Category: otc | Type: HUMAN OTC DRUG LABEL
Date: 20250715

ACTIVE INGREDIENTS: CALCIUM CARBONATE 750 mg/1 1
INACTIVE INGREDIENTS: ADIPIC ACID; DEXTROSE, UNSPECIFIED FORM; MAGNESIUM STEARATE; MALTODEXTRIN; FD&C RED NO. 40; STARCH, CORN; SUCRALOSE; FD&C YELLOW NO. 6; D&C YELLOW NO. 10

Best Choice Extra Strength Tropical Fruit Antacid 96 Tabs Drug Facts

Active ingredient (per tablet)

Calcium Carbonate USP 750mg

Purpose

Antacid

Uses

relieves

- heartburn
- acid indigestion
- sour stomach
- upset stomach associated with these symptoms

Warnings

Ask a doctor or pharmacist before use if you are

presently taking a prescription drug. Antacids may interact with certain prescription drug.

When using this product

- do not take more than 10 tablets in 24 hours
- if pregnant do not take more than 6 tablets in 24 hours
- do not use the maximum dosage for more than 2 weeks except under the advice and supervision of a doctor

Directions

- adults and children 12 years of age and over:chew 2-4 tablets as symptoms occur, or as directed by a doctor.
- do not take for symptoms that persist for more than 2 weeks unless advised by a doctor

Other information

- each tablet contains: elemental calcium 300mg
- Store below 30°C (86°F)

SAFETY SEALED: DO NOT USE IF PRINTED SEAL UNDER CAP IS TORN OR MISSING.

Inactive ingredients

adipic acid, dextrose, flavor, flavors, magnesium stearate, maltodextrin, red 40 lake, starch, sucralose, yellow 6 lake, yellow 10 lake.

Principal Display Panel

COMPARE TO THE ACTIVE INGREDIENT IN TUMS® EXTRA STRENGTH*

Best Choice®

NDC# 63941-022-96

EXTRA STRENGTH

Antacid Tablets

Calcium Carbonate 750 mg

Fast Relief of Upset Stomach, Heartburn and Acid Indigestion

ASSORTED TROPICAL FRUIT

96 CHEWABLE TABLETS

GLUTEN FREE

K PAREVE

Best Choice 100% Guaranteed www.bestchoicebrand.com

PROUDLY DISTRIBUTED BY:

VALU MERCHANDISERS, CO.

5000 KANSAS AVE

KANSAS CITY, KS 66106

*This product is not manufactured or distributed by GlaxoSmithKline, the distributor of TUMS®.